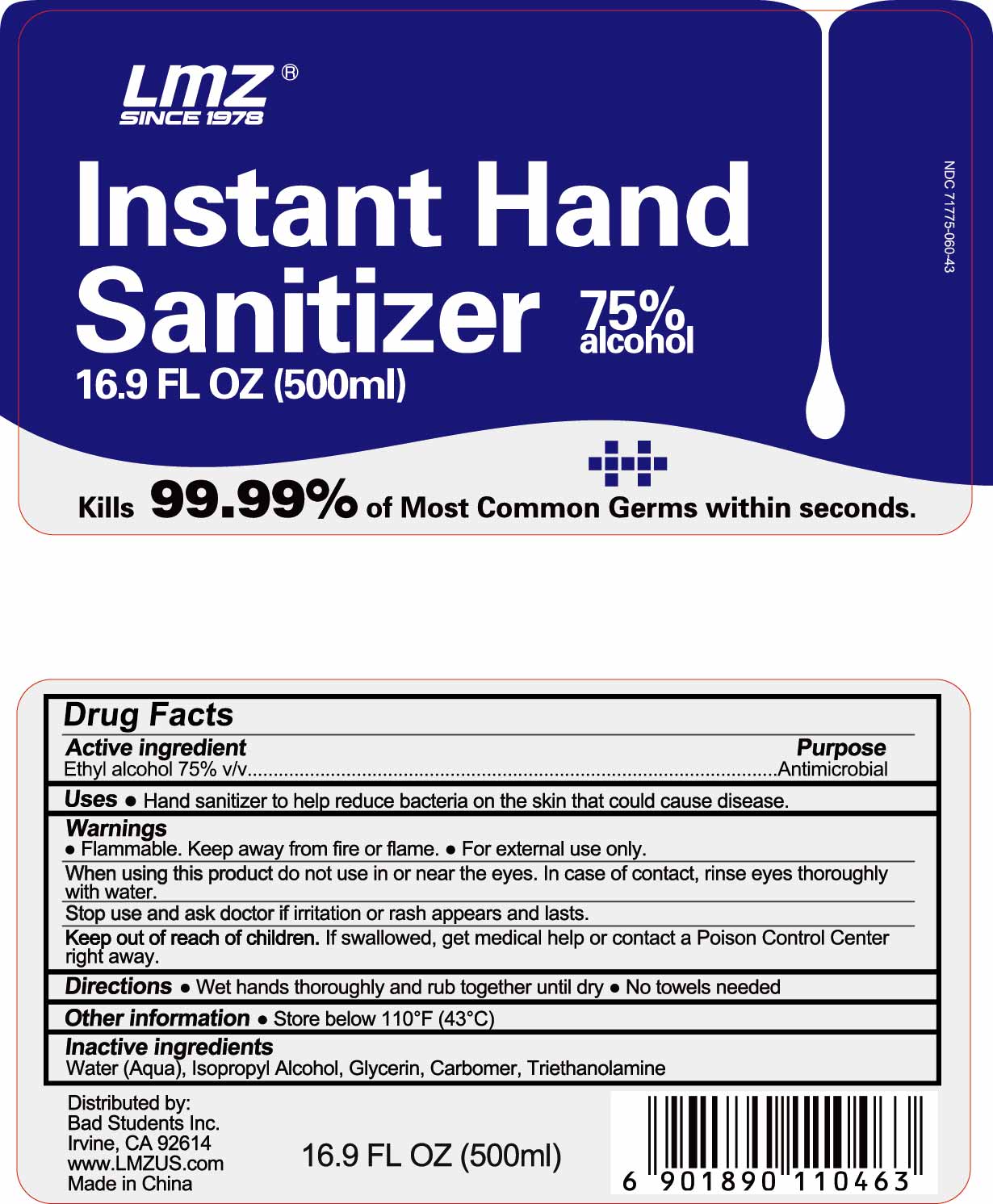 DRUG LABEL: Instant Hand Sanitizer
NDC: 71775-060 | Form: GEL
Manufacturer: LIUZHOU LMZ CO., LTD.
Category: otc | Type: HUMAN OTC DRUG LABEL
Date: 20200312

ACTIVE INGREDIENTS: ALCOHOL 75 mL/100 mL
INACTIVE INGREDIENTS: GLYCERIN; TROLAMINE; WATER; CARBOMER COPOLYMER TYPE B (ALLYL PENTAERYTHRITOL CROSSLINKED)

Active ingredient

Ethyl alcohol 75% v/v

Purpose

Antimicrobial

Uses

Hand sanitizer to help reduce bacteria on the skin that could cause disease.

Warnings

Flammable. Keep away from fire or flame. For external use only

When using this product do not use in or near the eyes. In case of contact, rinse eyes thoroughly with water.

Stop use and ask a doctor if irritation or rash appears and lasts

Keep out of reach of children. If swallowed, get medical help or contact a Poison Control Center right away.

Directions

- Wet hands thoroughly and rub together until dry
- No towels needed

Other information

- Store below 110°F (43°C)

Inactive ingredients

Water (Aqua), Isopropyl Alcohol, Glycerin, Carbomer, Triethanolamine

PACKAGE LABEL

16.9 FL OZ (500ml)

PACKAGE LABEL

Distributed by:

Bad Students Inc.

Irvine, CA 92614

www.LMZUS.com

Made in China